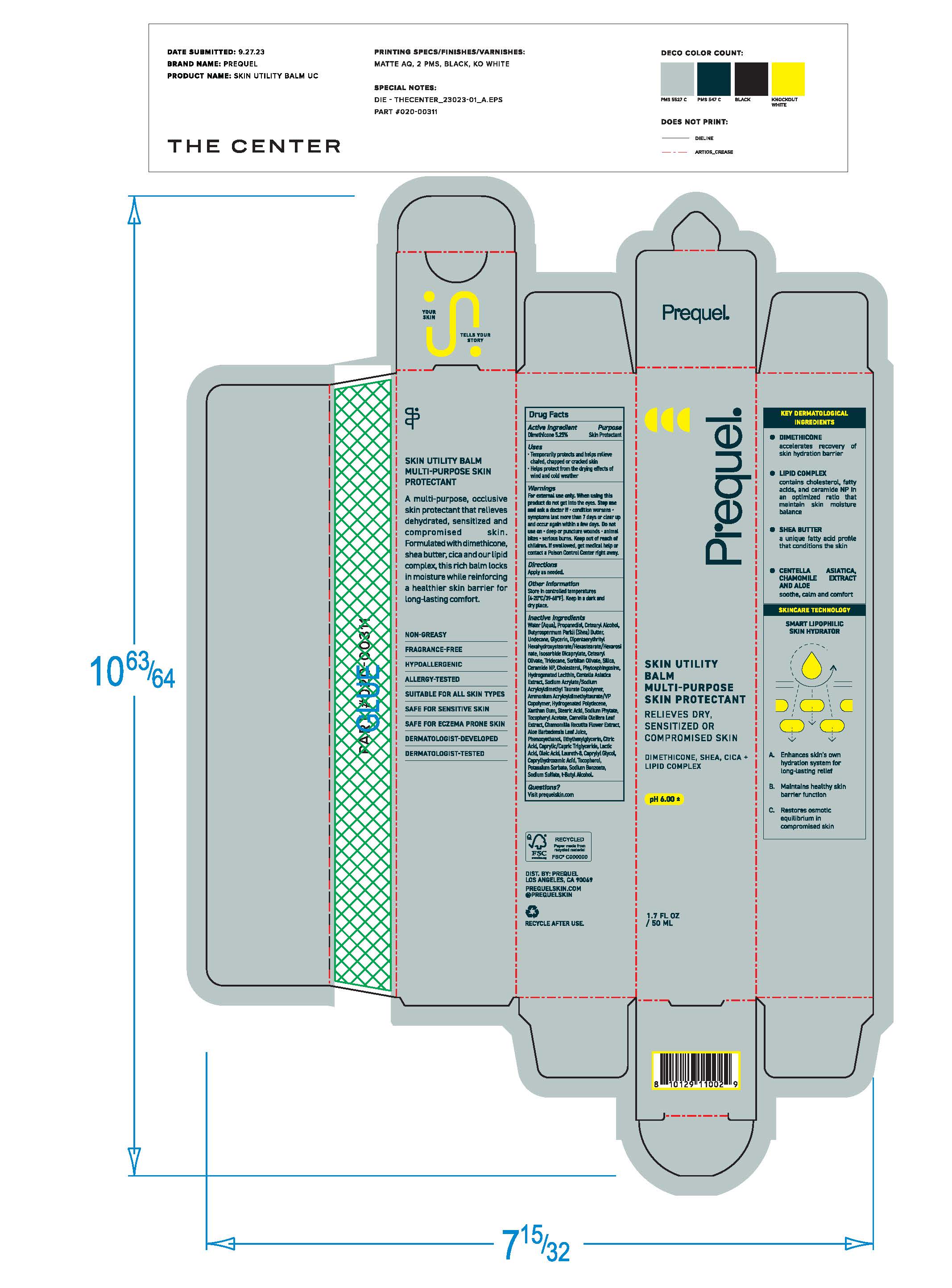 DRUG LABEL: Prequel Skin Utility Gel Multi-Purpose Skin Protectant
NDC: 82800-050 | Form: GEL
Manufacturer: The Center Brands, LLC
Category: otc | Type: HUMAN OTC DRUG LABEL
Date: 20241204

ACTIVE INGREDIENTS: GLYCERIN 20 mg/1 g
INACTIVE INGREDIENTS: WATER; DIMETHICONE; PANTHENOL; PEG/PPG-18/18 DIMETHICONE; HYDROXYETHYL ACRYLATE/SODIUM ACRYLOYLDIMETHYL TAURATE COPOLYMER (100000 MPA.S AT 1.5%); PANTHENYL ETHYL ETHER ACETATE; NIACINAMIDE; NARGENICIN; C15-23 ALKANE; PHENOXYETHANOL; DECYL GLUCOSIDE; TETRASODIUM GLUTAMATE DIACETATE; CITRIC ACID ACETATE; SODIUM HYDROXIDE

DRUG FACTS

Purpose

Skin Protectant

Active Ingredients

Glycerin 20%

Uses

Temporarily protects and helps releive chafed, chapper or cracked skin

Helps protect fomr the drying effects of wind and cold weather

Warnings

Fox external use only.

When using this product do not get into eyes

Stop use and ask a doctor if condition worsens

symptoms last more than 7 days or clear up and occur again within a few days

Keep out of reach of children. If swallowed, get medical help or contact a Poison Control Center right away.

Directions

Apply as needed.

Inactive ingredients

Water (Aqua), Dimethicone, Panthenol, PEG/PPG/18 Dimethicone Hydroxyethyl Acrylate/Sodium Acryloyldimethyl Tuarate Copolymer, Panthenyl Triacetate, Niacinamide, Naringenin, C15-23 Alkane, 1,2 Hexanediol, C13-14 Alkcane, Phenoxyethanol, Decyl Glucoside, Tetrasodium Glutamate Diacetate, Citric Acid, Sodium Hydroxide.

Other Information

• protect the product in this container from excessive
heat and direct sun

Questions?

Visit prequelskin.com